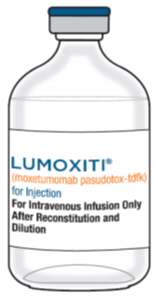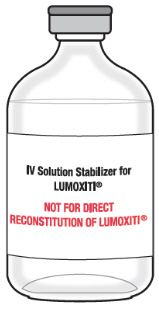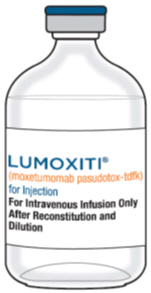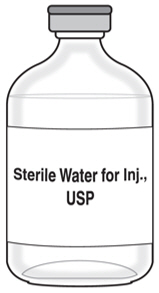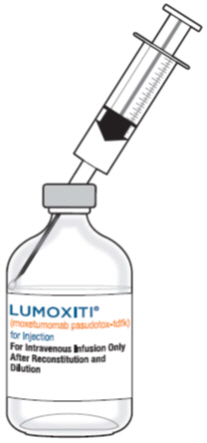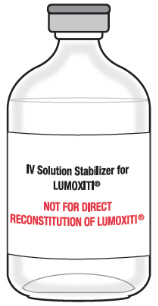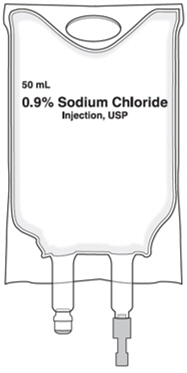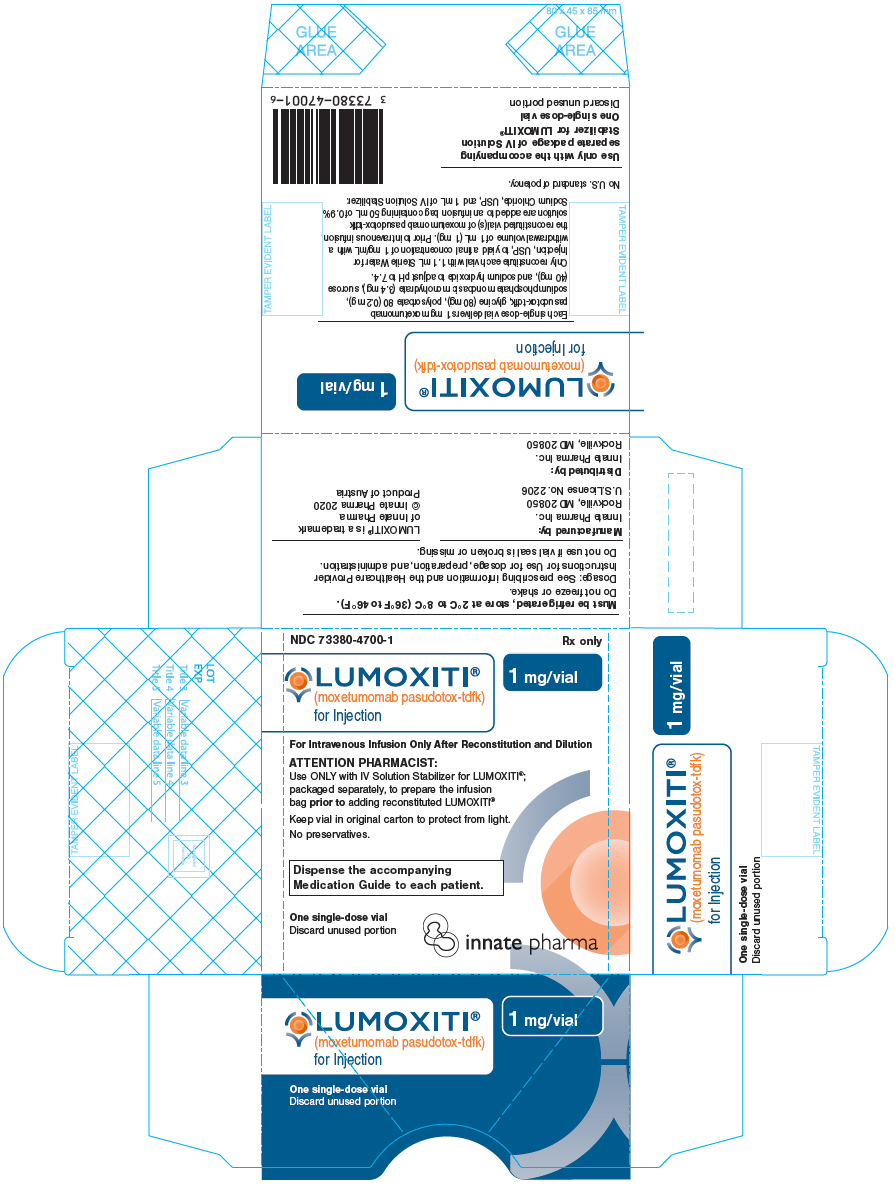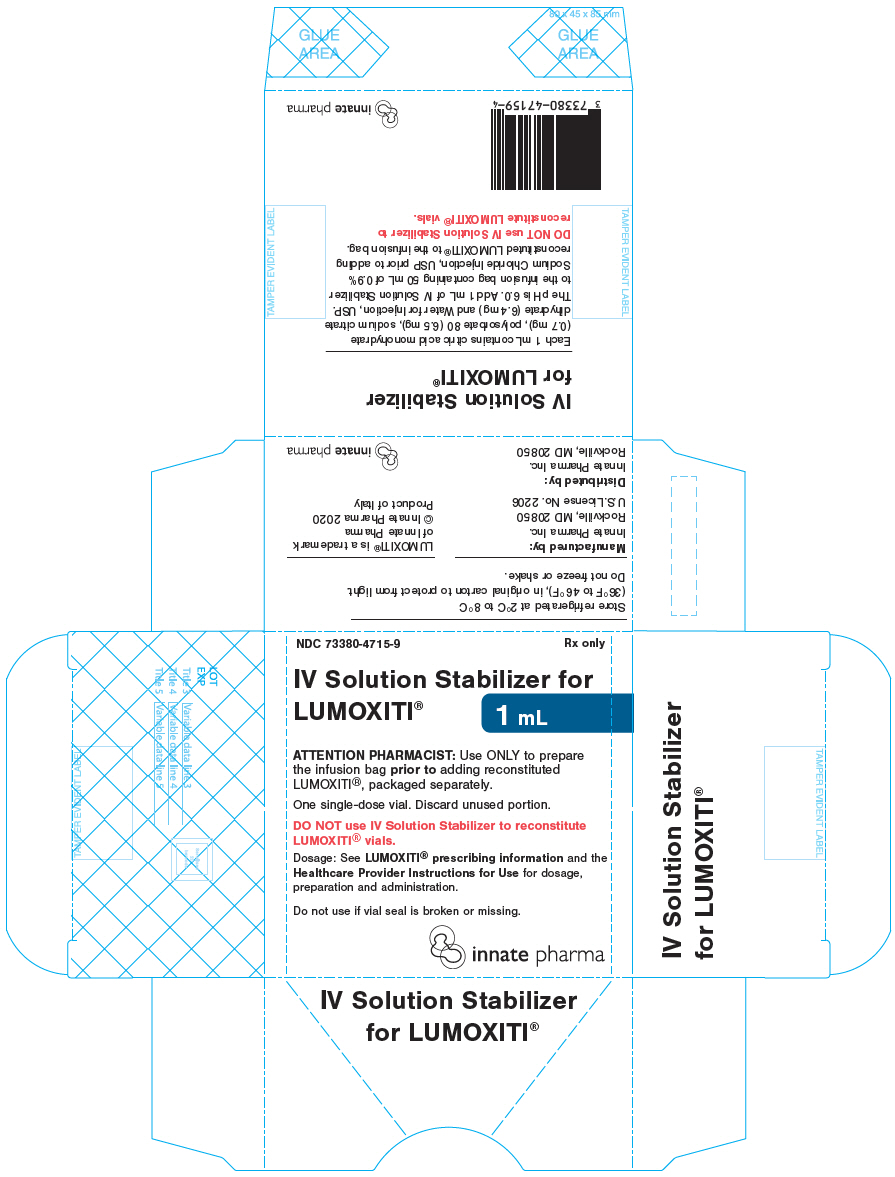 DRUG LABEL: LUMOXITI
NDC: 73380-4700 | Form: INJECTION, POWDER, LYOPHILIZED, FOR SOLUTION
Manufacturer: Innate Pharma, Inc.
Category: prescription | Type: HUMAN PRESCRIPTION DRUG LABEL
Date: 20200903

ACTIVE INGREDIENTS: MOXETUMOMAB PASUDOTOX 1 mg/1 mL
INACTIVE INGREDIENTS: GLYCINE 80 mg/1 mL; POLYSORBATE 80 0.2 mg/1 mL; SODIUM PHOSPHATE, MONOBASIC, MONOHYDRATE 3.4 mg/1 mL; SUCROSE 40 mg/1 mL

HIGHLIGHTS OF PRESCRIBING INFORMATION

These highlights do not include all the information needed to use LUMOXITI safely and effectively. See full prescribing information for LUMOXITI.
LUMOXITI® (moxetumomab pasudotox-tdfk) for injection, for intravenous use
Initial U.S. Approval: 2018

WARNING: CAPILLARY LEAK SYNDROME and HEMOLYTIC UREMIC SYNDROME

See full prescribing information for complete boxed warning.

- Capillary Leak Syndrome (CLS), including life-threatening cases, occurred in patients receiving LUMOXITI. Delay dosing or discontinue LUMOXITI as recommended. (2.3, 5.1)
- Hemolytic Uremic Syndrome (HUS), including life-threatening cases, occurred in patients receiving LUMOXITI. Discontinue LUMOXITI in patients with HUS. (2.3, 5.2)

1 INDICATIONS AND USAGE

LUMOXITI is a CD22-directed cytotoxin indicated for the treatment of adult patients with relapsed or refractory hairy cell leukemia (HCL) who received at least two prior systemic therapies, including treatment with a purine nucleoside analog (PNA). (1)

Limitations of Use

Not recommended in patients with severe renal impairment (CrCl ≤ 29 mL/min). (1)

2 DOSAGE AND ADMINISTRATION

- Recommended dosage: 0.04 mg/kg as an intravenous infusion over 30 minutes on Days 1, 3, and 5 of each 28-day cycle. (2.1)
- Maintain adequate hydration throughout treatment. (2.2)
- Consider low-dose aspirin on Days 1 to 8 of each 28-day cycle. (2.2)
- Premedicate with an acetaminophen antipyretic, antihistamine, and H2-receptor antagonist prior to all infusions. (2.2)
- See full prescribing information for instructions on reconstitution of lyophilized cake or powder, and preparation and administration of reconstituted drug. (2.4)

3 DOSAGE FORMS AND STRENGTHS

For injection: 1 mg lyophilized cake or powder in a single-dose vial for reconstitution and further dilution. (3)

4 CONTRAINDICATIONS

None. (4)

5 WARNINGS AND PRECAUTIONS

- Renal Toxicity: Monitor for changes in renal function prior to each infusion and as clinically indicated. Delay dosing until recovery. (5.3)
- Infusion Related Reactions: Pre-medicate and if a severe infusion related reaction occurs, interrupt the LUMOXITI infusion and institute appropriate medical management. (5.4)
- Electrolyte Abnormalities: Monitor serum electrolytes prior to each dose and on Day 8 of each treatment cycle. Monitoring mid-cycle is also recommended. (5.5)

6 ADVERSE REACTIONS

Most common (≥ 20%) adverse reactions are infusion related reactions, edema, nausea, fatigue, headache, pyrexia, constipation, anemia, and diarrhea. Most common (≥ 50%) laboratory abnormalities are creatinine increased, ALT increased, hypoalbuminemia, AST increased, hypocalcemia, and hypophosphatemia. (6.1)

To report SUSPECTED ADVERSE REACTIONS, contact Innate Pharma at 1-888-501-0998 or FDA at 1-800-FDA-1088 or www.fda.gov/medwatch.

8 USE IN SPECIFIC POPULATIONS

Lactation: Advise women not to breastfeed. (8.2)

FULL PRESCRIBING INFORMATION

WARNING: CAPILLARY LEAK SYNDROME and HEMOLYTIC UREMIC SYNDROME

- Capillary Leak Syndrome (CLS), including life-threatening cases, occurred in patients receiving LUMOXITI. Monitor weight and blood pressure; check labs, including albumin, if CLS is suspected. Delay dosing or discontinue LUMOXITI as recommended [see Dosage and Administration (2.3) and Warnings and Precautions (5.1)].
- Hemolytic Uremic Syndrome (HUS), including life-threatening cases, occurred in patients receiving LUMOXITI. Monitor hemoglobin, platelet count, serum creatinine, and ensure adequate hydration. Discontinue LUMOXITI in patients with HUS [see Dosage and Administration (2.3) and Warnings and Precautions (5.2)].

1 INDICATIONS AND USAGE

LUMOXITI is indicated for the treatment of adult patients with relapsed or refractory hairy cell leukemia (HCL) who received at least two prior systemic therapies, including treatment with a purine nucleoside analog (PNA).

Limitations of Use

LUMOXITI is not recommended in patients with severe renal impairment (CrCl ≤ 29 mL/min) [see Dosage and Administration (2.3), Warnings and Precautions (5.3), and Use in Specific Populations (8.5)].

2 DOSAGE AND ADMINISTRATION

2.1 Recommended Dosage

The recommended dose of LUMOXITI is 0.04 mg/kg administered as a 30-minute intravenous infusion on Days 1, 3, and 5 of each 28-day cycle. Continue LUMOXITI treatment for a maximum of 6 cycles, disease progression, or unacceptable toxicity.

2.2 Recommended Concomitant Treatment

Hydration

Intravenously administer 1 L of isotonic solution (e.g., 5% Dextrose Injection, USP and 0.45% or 0.9% Sodium Chloride Injection, USP) over 2-4 hours before and after each LUMOXITI infusion. Administer 0.5 L to patients under 50 kg.

Advise all patients to adequately hydrate with up to 3 L (twelve 8-oz glasses) of oral fluids (e.g., water, milk, or juice) per 24 hours on Days 1 through 8 of each 28-day cycle. In patients under 50 kg, up to 2 L (eight 8-oz glasses) per 24 hours is recommended.

Monitor fluid balance and serum electrolytes to avoid fluid overload and/or electrolyte abnormalities [see Warnings and Precautions (5.2, 5.5)].

Thromboprophylaxis

Consider low-dose aspirin on Days 1 through 8 of each 28-day cycle.

Monitor for signs and symptoms of thrombosis [see Warnings and Precautions (5.2)].

Premedication

Premedicate 30-90 minutes prior to each LUMOXITI infusion with:

- An antihistamine (e.g., hydroxyzine or diphenhydramine)
- Acetaminophen antipyretic
- A histamine-2 receptor antagonist (e.g., ranitidine, famotidine, or cimetidine)

If a severe infusion related reaction occurs, interrupt the LUMOXITI infusion and institute appropriate medical management. Administer an oral or intravenous corticosteroid approximately 30 minutes before resuming, and before each LUMOXITI infusion thereafter [see Warnings and Precautions (5.4)].

Post-infusion Medication

- Consider oral antihistamines and antipyretics for up to 24 hours following LUMOXITI infusions.
- An oral corticosteroid (e.g., 4 mg dexamethasone) is recommended to decrease nausea and vomiting.
- Maintain adequate oral fluid intake.

2.3 Monitoring to Assess Safety

Manage adverse reactions by withholding and/or discontinuing LUMOXITI as described below.

Identify Capillary Leak Syndrome (CLS) and Hemolytic Uremic Syndrome (HUS) based on clinical presentation (see Table 1).

Table 1: Monitoring for CLS and HUS
 | CLS | HUS
Monitoring Parameter | Before every infusion, check:; - Weight - Blood pressure | Before every infusion, check:; - Hemoglobin levels - Platelet count - Serum creatinine
Assessment | - If weight has increased by 5.5 pounds (2.5 kg) or 5% or greater from Day 1 of the cycle and the patient is hypotensive, promptly check for peripheral edema, hypoalbuminemia, and respiratory symptoms, including shortness of breath and cough. - If CLS is suspected, check for a decrease in oxygen saturation and evidence of pulmonary edema and/or serosal effusions. | If HUS is suspected, promptly check blood LDH, indirect bilirubin, and blood smear schistocytes for evidence of hemolysis.
Adverse reactions graded by the National Cancer Institute Common Terminology Criteria for Adverse Events (NCI CTCAE) version 4.03.

Capillary Leak Syndrome (CLS)

Patients who experience Grade 2 or higher CLS should receive appropriate supportive measures, including treatment with oral or intravenous corticosteroids, with monitoring of weight, albumin levels, and blood pressure until resolution [see Warnings and Precautions (5.1)].

Table 2: CLS Grading and Management Guidance
CLS Grade | LUMOXITI Dosing
Grade 2 Symptomatic; medical intervention indicated | Delay dosing until recovery of symptoms.
Grade 3 Severe symptoms; medical intervention indicated | Discontinue LUMOXITI.
Grade 4 Life-threatening consequences; urgent intervention indicated | Discontinue LUMOXITI.
Per National Cancer Institute Common Terminology Criteria for Adverse Events (NCI CTCAE) version 4.03.

Hemolytic Uremic Syndrome (HUS)

Discontinue LUMOXITI in patients with HUS. Treat with appropriate supportive measures and fluid replacement, with monitoring of blood chemistry, complete blood counts, and renal function until resolution [see Warnings and Precautions (5.2)].

Increased Creatinine

For patients with baseline serum creatinine within normal limits, delay dosing for Grade 2 or higher creatinine increases (greater than 1.5-times baseline or the upper limit of normal). Resume LUMOXITI upon recovery to Grade 1 (1- to 1.5-times baseline, or between the upper limit of normal and 1.5-times the upper limit of normal).

For patients with baseline serum creatinine of Grades 1 or 2, delay dosing for creatinine increases to Grade 3 or higher (greater than 3-times baseline or the upper limit of normal). Resume LUMOXITI upon recovery to baseline grade or lower [see Warnings and Precautions (5.3)].

2.4 Instructions for Reconstitution, Dilution, and Administration

LUMOXITI must be reconstituted and diluted by a healthcare provider using aseptic technique. Refer to the Healthcare Provider Instructions for Use for LUMOXITI for full reconstitution, dilution, and administration information.

Step 1: Calculate Dose

- Calculate the dose (mg) and the number of LUMOXITI vials (1 mg/vial) to be reconstituted. The final concentration of the reconstituted LUMOXITI solution is 1 mg/mL.
  - DO NOT round down for partial vials.
- Individualize dosing based on the patient's actual body weight prior to the first dose of the first treatment cycle.
  - A change in dose should only be made between cycles when a change in weight of greater than 10% is observed from the weight used to calculate the first dose of the first treatment cycle. No change in dose should be made during a particular cycle.

Step 2: Reconstitution

Reconstitute LUMOXITI vials with Sterile Water for Injection, USP only.

- Reconstitute each LUMOXITI (1 mg/vial) with 1.1 mL Sterile Water for Injection, USP. The resulting 1 mg/mL solution allows a withdrawal volume of 1 mL.
  - Direct the Sterile Water for Injection, USP along the walls of the vial and not directly at the lyophilized cake or powder.
  - DO NOT reconstitute LUMOXITI vials with the IV Solution Stabilizer.
- Gently swirl the vial until completely dissolved. Invert the vial to ensure all cake or powder in the vial is dissolved. Do not shake.
- Visually inspect that the reconstituted solution is clear to slightly opalescent, colorless to slightly yellow, and free from visible particles. Do not use if solution is cloudy, discolored, or contains any particles.
- Use reconstituted solution immediately. Do not store reconstituted LUMOXITI vials. See Table 3 for storage times and conditions for the reconstituted solution.

Step 3: Dilution

Add the IV Solution Stabilizer to the infusion bag prior to adding LUMOXITI solution to the infusion bag. Vial of IV Solution Stabilizer is packaged separately.

- Obtain a 50 mL 0.9% Sodium Chloride Injection, USP infusion bag.
- Add 1 mL IV Solution Stabilizer to the infusion bag containing 50 mL 0.9% Sodium Chloride Injection, USP.
  - Only one vial of IV Solution Stabilizer should be used per administration of LUMOXITI.
  - Gently invert the bag to mix the solution. Do not shake.
- Withdraw the required volume (calculated from Step 1) of LUMOXITI solution from the reconstituted vial(s).
  - Inject LUMOXITI into the infusion bag containing 50 mL 0.9% Sodium Chloride Injection, USP and 1 mL IV Solution Stabilizer.
  - Gently invert the bag to mix the solution. Do not shake.
- Discard any partially used or empty vials of LUMOXITI and IV Solution Stabilizer.
- See Table 3 for storage times and conditions for the diluted solution.

Step 4: Administration Instructions

For intravenous infusion only.

- Administer the diluted solution intravenously over 30 minutes.
- Do not mix LUMOXITI, or administer as an infusion with other medicinal products.
- After the infusion, flush the intravenous administration line with of 0.9% Sodium Chloride Injection, USP at the same rate as the infusion. This ensures that the full LUMOXITI dose is delivered.

Table 3: Storage Times and Conditions for Reconstituted and Diluted LUMOXITI Solution
Reconstituted Solution | Diluted LUMOXITI Solution in Infusion Bag
Reconstituted Solution | After Dilution | Administration
LUMOXITI does not contain bacteriostatic preservatives. Use reconstituted solution immediately. DO NOT STORE reconstituted LUMOXITI vials. | Use diluted solution immediately or after storage at room temperature (20°C to 25°C; 68°F to 77°F) for up to 4 hours or store refrigerated at 2°C to 8°C (36°F to 46°F) for up to 24 hours. PROTECT FROM LIGHT. DO NOT FREEZE. DO NOT SHAKE. | If the diluted solution is refrigerated (2°C to 8°C; 36°F to 46°F), allow it to equilibrate at room temperature (20°C to 25°C; 68°F to 77°F) for no more than 4 hours prior to administration. Administer diluted solution within 24 hours of reconstitution as a 30-minute infusion. PROTECT FROM LIGHT.

3 DOSAGE FORMS AND STRENGTHS

For injection: 1 mg as a white to off-white lyophilized cake or powder in a single-dose vial for reconstitution and further dilution.

4 CONTRAINDICATIONS

None.

5 WARNINGS AND PRECAUTIONS

5.1 Capillary Leak Syndrome (CLS)

Capillary leak syndrome (CLS), including life-threatening cases, has been reported among patients treated with LUMOXITI and is characterized by hypoalbuminemia, hypotension, symptoms of fluid overload, and hemoconcentration. In the combined safety database of HCL patients treated with LUMOXITI, CLS occurred in 34% (44/129) of patients, including Grade 2 in 23% (30/129), Grade 3 in 1.6% (2/129), and Grade 4 in 2% (3/129).

Most cases of CLS occurred in the first 8 days (range: 1 to 19) of a treatment cycle, however, cases have also been reported on other days throughout the cycle. The median time to resolution of CLS was 12 days (range: 1 to 53).

Monitor patient weight and blood pressure prior to each LUMOXITI infusion and as clinically indicated during treatment. Assess patients for signs and symptoms of CLS, including weight gain (increase in 5.5 pounds (2.5 kg) or ≥ 5% from Day 1 of current cycle), hypotension, peripheral edema, shortness of breath or cough, and pulmonary edema and/or serosal effusions. In addition, the following changes in laboratory parameters may help identify CLS: hypoalbuminemia, elevated hematocrit, leukocytosis, and thrombocytosis [see Dosage and Administration (2.3)].

CLS may be life-threatening or fatal if treatment is delayed. Counsel patients to seek immediate medical attention should signs or symptoms of CLS occur at any time. Patients who develop CLS should receive appropriate supportive measures, including concomitant oral or intravenous corticosteroids, and hospitalization as clinically indicated. Withhold LUMOXITI for Grade 2 CLS until resolution, and permanently discontinue for Grade ≥ 3 CLS [see Dosage and Administration (2.3)].

5.2 Hemolytic Uremic Syndrome (HUS)

Hemolytic Uremic Syndrome (HUS), including life threatening cases, has been reported in patients treated with LUMOXITI and is characterized by the triad of microangiopathic hemolytic anemia, thrombocytopenia, and progressive renal failure. In the combined safety database of HCL patients treated with LUMOXITI, HUS occurred in 7% (9/129) of patients, including Grade 3 in 3% (4/129) and Grade 4 in 0.8% (1/129).

Most cases of HUS occurred in the first 9 days (range: 1 to 16) of a treatment cycle, however, cases have also been reported on other days throughout the cycle. The median time to resolution of HUS was 11.5 days (range: 2 to 44). All cases resolved, including those who discontinued LUMOXITI.

Avoid LUMOXITI in patients with prior history of severe thrombotic microangiopathy (TMA) or HUS. Administer prophylactic intravenous fluids before and after LUMOXITI infusions [see Dosage and Administration (2.2)]. In Study 1053, patients with a platelet count ≥ 100,000/mm^3 received low-dose aspirin on Days 1 through 8 of each 28-day cycle for prophylaxis of thrombosis.

Monitor blood chemistry and complete blood counts prior to each dose and on Day 8 of each treatment cycle. Monitoring mid-cycle is also recommended. Consider the diagnosis of HUS in patients who develop hemolytic anemia, worsening or sudden onset of thrombocytopenia, increase in creatinine levels, elevation of bilirubin and/or LDH, and have evidence of hemolysis based on peripheral blood smear schistocytes [see Dosage and Administration (2.3)].

The events of HUS may be life-threatening if treatment is delayed with increased risk of progressive renal failure requiring dialysis. If HUS is suspected initiate appropriate supportive measures, including fluid repletion, hemodynamic monitoring, and consider hospitalization as clinically indicated. Discontinue LUMOXITI in patients with HUS [see Dosage and Administration (2.3)].

5.3 Renal Toxicity

Renal toxicity has been reported in patients treated with LUMOXITI therapy. In the combined safety database of HCL patients treated with LUMOXITI, 26% (34/129) reported adverse events of renal toxicity, including acute kidney injury (2.3%), renal failure (2.3%), renal impairment (1.6%), serum creatinine increased (17%), and proteinuria (8%). Grade 3 acute kidney injury occurred in 1.6% (2/129) of patients. All other events were mild to moderate in severity.

Based on laboratory findings, during treatment, serum creatinine increased by two or more grades from baseline in 22% (29/129) of patients, including increases of Grade 3 in 1.6% (2/129) of patients. At the end of treatment, serum creatinine levels remained elevated at 1.5- to 3-times the upper limit of normal in 5% of patients. Patients who experience HUS, those ≥ 65 years of age, or those with baseline renal impairment may be at increased risk for worsening of renal function following treatment with LUMOXITI [see Use in Specific Populations (8.5)].

Monitor renal function prior to each infusion of LUMOXITI, and as clinically indicated throughout treatment. Delay LUMOXITI dosing in patients with Grade ≥ 3 elevations in creatinine, or upon worsening from baseline by ≥ 2 grades [see Dosage and Administration (2.3)].

5.4 Infusion Related Reactions

Infusion related reactions occurred in patients treated with LUMOXITI, and were defined as the occurrence of any one of the following events on the day of study drug infusion: chills, cough, dizziness, dyspnea, feeling hot, flushing, headache, hypertension, hypotension, infusion related reaction, myalgia nausea, pyrexia, sinus tachycardia, tachycardia, vomiting, or wheezing. In Study 1053, infusion related reactions occurred in 50% (40/80) of patients. Grade 3 infusion related events as defined, occurred in 3.8% (3/80) of LUMOXITI-treated patients. The most frequently reported infusion related events were nausea (15%), pyrexia (14%), chills (14%), vomiting (11%), headache (9%), and infusion related reaction (9%).

Infusion related reactions may occur during any cycle of treatment with LUMOXITI. Prior to each dose of LUMOXITI, premedicate with antihistamines and antipyretics. If a severe infusion related reaction occurs, interrupt the LUMOXITI infusion and institute appropriate medical management. Administer an oral or intravenous corticosteroid approximately 30 minutes before resuming, or before the next LUMOXITI infusion [see Dosage and Administration (2.2)].

5.5 Electrolyte Abnormalities

In the combined safety database of HCL patients treated with LUMOXITI, electrolyte abnormalities occurred in 57% (73/129) of patients with the most common electrolyte abnormality being hypocalcemia occurring in 25% of patients. Grade 3 electrolyte abnormalities occurred in 14% (18/129) of patients and Grade 4 electrolyte abnormalities occurred in 0.8% (1/129) of patients. Electrolyte abnormalities co-occurred in the same treatment cycle with CLS, HUS, fluid retention, or renal toxicity in 37% (48/129) of patients.

Monitor serum electrolytes prior to each dose and on Day 8 of each treatment cycle. Monitoring mid-cycle is also recommended.

6 ADVERSE REACTIONS

The following adverse reactions are discussed in greater detail in other sections of the labeling.

- Capillary Leak Syndrome [see Warnings and Precautions (5.1)]
- Hemolytic Uremic Syndrome [see Warnings and Precautions (5.2)]
- Renal Toxicity [see Warnings and Precautions (5.3)]
- Infusion Related Reactions [see Warnings and Precautions (5.4)]
- Electrolyte Abnormalities [see Warnings and Precautions (5.5)]

6.1 Clinical Trials Experience

As clinical trials are conducted under widely varying conditions, adverse reaction rates observed in the clinical trials of a drug cannot be directly compared to rates in the clinical trials of another drug and may not reflect the rates observed in practice.

The safety data described in this section reflect exposure to LUMOXITI in 80 patients with previously treated HCL in Study 1053 [see Clinical Studies (14)]. Patients received LUMOXITI 0.04 mg/kg as an intravenous infusion over 30 minutes on Days 1, 3, and 5 of each 28-day cycle for a maximum of 6 cycles or until disease progression or unacceptable toxicity.

The median duration of treatment with LUMOXITI was 5.7 months (range: 0.9 to 6.7), with a median of 6 treatment cycles started in each patient.

The most common non-laboratory adverse reactions (≥ 20%) of any grade were infusion related reactions, edema, nausea, fatigue, headache, pyrexia, constipation, anemia, and diarrhea. The most common Grade 3 or 4 adverse reactions (reported in at least ≥ 5% of patients) were hypertension, febrile neutropenia, and HUS.

The most common laboratory abnormalities (≥ 20%) of any grade were creatinine increased, ALT increased, hypoalbuminemia, AST increased, hypocalcemia, hypophosphatemia, hemoglobin decreased, neutrophil count decreased, hyponatremia, blood bilirubin increased, hypokalemia, GGT increased, hypomagnesemia, platelet count decreased, hyperuricemia, and alkaline phosphate increased.

Adverse reactions resulting in permanent discontinuation of LUMOXITI occurred in 15% (12/80) of patients. The most common adverse reaction leading to LUMOXITI discontinuation was HUS (5%). The most common adverse reaction resulting in dose delays, omissions, or interruptions was pyrexia (3.8%).

Tables 4 and 5 present the frequency category of adverse reactions and key laboratory abnormalities observed in patients with relapsed or refractory HCL treated with LUMOXITI.

Table 4: Adverse Reactions [Per National Cancer Institute Common Terminology Criteria for Adverse Events (NCI CTCAE) version 4.03.] in ≥ 20% (All Grades) of Patients with HCL in Study 1053
 | LUMOXITI N=80
 | All Grades (%) | Grade 3 (%)
General Disorders and Administration Site Conditions
Edema peripheral | 39 | -
Fatigue | 34 | -
Pyrexia | 31 | 1.3
Gastrointestinal Disorders
Nausea | 35 | 2.5
Constipation | 23 | -
Diarrhea | 21 | -
Injury, Poisoning, and Procedural Complications
Infusion related reactions [Infusion related reactions: includes patients who were reported to have one or more infusion event that may be infusion-related on the day of study drug infusion.] | 50 | 3.8
Nervous System Disorders
Headache | 33 | -
Blood and Lymphatic System Disorders
Anemia | 21 | 10

Fluid retention occurred in 63% (50/80) of patients treated with LUMOXITI in Study 1053, including Grade 3 in 1.3% (1/80) of patients. Fluid retention included all preferred terms of edema peripheral (39%), face edema (14%), abdominal distension (13%), weight increased (8%), pleural effusion (6%), edema (5%), peripheral swelling (5%), localized edema (3.8%), ascites (1.3%), fluid overload (1.3%), fluid retention (1.3%), and pericardial effusion (1.3%). Of the fifty patients with fluid retention, 29% of patients required diuretics.

Ocular adverse events occurred, including: blurred vision (9%), dry eye (8%), cataracts (5%), ocular discomfort and/or pain (4%), ocular swelling/periorbital edema (4%), conjunctivitis (1.3%), conjunctival hemorrhage (1.3%), and ocular discharge (1.3%).

Table 5: Laboratory Abnormalities [Per National Cancer Institute Common Terminology Criteria for Adverse Events (NCI CTCAE) version 4.03 and based on laboratory measurements worsening from baseline] in ≥ 20% (All Grades) Reported in Patients with HCL in Study 1053
 | LUMOXITI N=80
 | All Grades (%) | Grade 3 (%) | Grade 4 (%)
Hematology
Hemoglobin decreased | 43 | 15 | -
Neutrophil count decreased | 41 | 11 | 20
Platelet count decreased | 21 | 11 | 3.8
Chemistry
Creatinine increased | 96 | 2.5 | -
ALT increased | 65 | 3.8 | -
Hypoalbuminemia | 64 | 1.3 | -
AST increased | 55 | 1.3 | -
Hypocalcemia | 54 | - | -
Hypophosphatemia | 53 | 14 | -
Hyponatremia | 41 | 8.8 | -
Blood Bilirubin increased | 30 | 1.3 | -
Hypokalemia | 25 | 1.3 | 1.3
GGT increased | 25 | - | -
Hypomagnesemia | 23 | 1.3 | -
Hyperuricemia | 21 | - | 2.5
Alkaline phosphatase increased | 20 | - | -
ALT=alanine aminotransferase; AST=aspartate aminotransferase; GGT=gamma glutamyl transferase

6.2 Immunogenicity

As with all therapeutic proteins, there is potential for immunogenicity. The detection of antibody formation is highly dependent on the sensitivity and specificity of the assay. Additionally, the observed incidence of antibody (including neutralizing antibody) positivity in an assay may be influenced by several factors, including assay methodology, sample handling, timing of sample collection, concomitant medications, and underlying disease. For these reasons, comparison of the incidence of antibodies to moxetumomab pasudotox-tdfk in the studies described below with the incidence of antibodies in other studies or to other products may be misleading.

The immunogenicity of LUMOXITI was evaluated using electrochemiluminescent (ECL)-based immunoassay to test for anti-moxetumomab pasudotox-tdfk antibodies (ADA). For patients whose serum tested positive for ADA, a cell-based assay was performed to detect neutralizing antibodies (nAb). In Study 1053, 59% (45/76) of patients tested positive for ADA prior to any treatment with moxetumomab pasudotox-tdfk. Seventy out of 80 subjects tested ADA positive at any point during the study and were subsequently tested for nAb. The results showed that 67 of 70 subjects were nAb-positive. Among these 67 patients who tested nAb-positive, 99% (66/67) had ADA specific to the PE38 binding domain, and 54% (36/67) also had ADA specific to the CD22 binding domain. In 41 out of 73 patients who had baseline and post-baseline ADA results, the median fold increase from baseline (Cycle 1, Day 1) in ADA titer was 3.75- (range: 0 to 240), 54- (range: 0 to 2560), 120- (range: 0 to 1920), and 128- (range: 0 to 2560) fold at Cycles 2, 3, 5, and end-of-treatment, respectively. Patients who tested positive for ADA had decreased systemic moxetumomab pasudotox-tdfk concentrations [see Clinical Pharmacology (12.3)].

8 USE IN SPECIFIC POPULATIONS

8.1 Pregnancy

Risk Summary

Based on its mechanism of action and findings in non-pregnant female animals, LUMOXITI is expected to cause maternal and embryo-fetal toxicity when administered to a pregnant woman [see Clinical Pharmacology (12.1) and Nonclinical Toxicology (13.2)]. There are no available data on LUMOXITI use in pregnant women to inform a drug-associated risk of major birth defects and miscarriage. Animal reproduction or developmental toxicity studies have not been conducted with LUMOXITI. Advise pregnant women of the potential risk to a fetus.

The estimated background risk of major birth defects and miscarriage for the indicated population is unknown. All pregnancies have a background risk of birth defect, loss, or other adverse outcomes. In the U.S. general population, the estimated background risk of major birth defects and miscarriage in clinically recognized pregnancies is 2-4% and 15-20%, respectively.

8.2 Lactation

Risk Summary

No data are available regarding the presence of moxetumomab pasudotox-tdfk in human milk, the effects on the breastfed child, or the effects on milk production. The developmental and health benefits of breastfeeding should be considered along with the mother's clinical need for LUMOXITI and any potential adverse effects on the breastfed child from LUMOXITI or from the underlying maternal condition.

8.3 Females and Males of Reproductive Potential

Contraception

Females

To avoid potential exposure to the fetus, women of reproductive potential should use effective contraception during treatment with LUMOXITI and for at least 30 days after the last dose is received. Verify the pregnancy status of females of reproductive potential prior to initiating LUMOXITI.

8.4 Pediatric Use

Safety and effectiveness have not been established in pediatric patients.

8.5 Geriatric Use

In the combined safety database of HCL patients treated with LUMOXITI, 31% (40/129) of patients treated with LUMOXITI were 65 years of age or older and 8% (10/129) were 75 years of age or older. Exploratory analyses across this population suggest a higher incidence of adverse reactions leading to drug discontinuation (23% versus 7%) and renal toxicity (40% versus 20%) for patients 65 years of age or older as compared to those younger than 65 years. Clinical studies of LUMOXITI did not include sufficient numbers of subjects aged 65 and over to determine whether there were differences in efficacy between younger and older patients.

11 DESCRIPTION

Moxetumomab pasudotox-tdfk is a CD22-directed cytotoxin. Moxetumomab pasudotox-tdfk is composed of a recombinant, murine immunoglobulin variable domain genetically fused to a truncated form of Pseudomonas exotoxin, PE38, that inhibits protein synthesis. Moxetumomab pasudotox-tdfk has an approximate molecular weight of 63 kDa and is produced in E. coli cells by recombinant DNA technology. During the moxetumomab pasudotox-tdfk manufacturing process, fermentation is carried out in nutrient medium containing the antibiotic kanamycin. However, kanamycin is cleared in the manufacturing process and is not detectable in the final product.

LUMOXITI (moxetumomab pasudotox-tdfk) for injection is supplied as a sterile, preservative-free, white to off-white lyophilized cake or powder in a single-dose vial for reconstitution and dilution prior to intravenous infusion. Each single-dose vial contains 1 mg moxetumomab pasudotox-tdfk, glycine (80 mg), polysorbate 80 (0.2 mg), sodium phosphate monobasic monohydrate (3.4 mg), sucrose (40 mg), and sodium hydroxide to adjust pH to 7.4. After reconstitution with 1.1 mL Sterile Water for Injection, USP, the resulting 1 mg/mL solution allows a withdrawal volume of 1 mL. Prior to intravenous infusion, the reconstituted vial(s) of solution are added to an infusion bag containing 50 mL of 0.9% Sodium Chloride Injection, USP and 1 mL of IV Solution Stabilizer.

IV Solution Stabilizer is a sterile, preservative-free, colorless to slightly yellow, clear solution free from visible particles and supplied in a single-dose vial. Each vial contains 1 mL solution. Each vial contains citric acid monohydrate (0.7 mg), polysorbate 80 (6.5 mg), sodium citrate dihydrate (6.4 mg), and Water for Injection, USP. The pH is 6.0.

The LUMOXITI and IV Solution Stabilizer vial stoppers are not made with natural rubber latex.

12 CLINICAL PHARMACOLOGY

12.1 Mechanism of Action

Moxetumomab pasudotox-tdfk is a CD22-directed cytotoxin. Moxetumomab pasudotox-tdfk binds CD22 on the cell surface of B-cells and is internalized. Moxetumomab pasudotox-tdfk internalization results in ADP-ribosylation of elongation factor 2, inhibition of protein synthesis, and apoptotic cell death.

12.2 Pharmacodynamics

The presence of moxetumomab pasudotox-tdfk may interfere with detection of cellular CD22, therefore, total peripheral blood B-cell counts (including normal B cells and HCL cells) were quantified using a standard assay for CD19+ B cells as a surrogate. In patients with HCL, treatment with LUMOXITI at the approved recommended dosage resulted in a reduction of circulating CD19+ B cells. The circulating CD19+ B cells on Day 8 were reduced by 89% from baseline following the first three infusions of LUMOXITI. B cell reduction was sustained for at least 1-month post-treatment.

Total counts of CD3+ T cells, CD4+ T cells, CD8+ T cells, and CD16+/CD56 Natural Killer cells and quantitative immunoglobulin (Ig) A, G, and M levels were evaluated throughout the course of treatment. On Day 8, median cell counts were reduced from baseline for the following populations: CD3+ T cells (-21%), CD4+ T cells (-20%), CD8+ T cells (-23%), and CD16+/CD56 Natural Killer cells (-47%). All monitored cell counts returned to, or were elevated above baseline levels on Day 29 and thereafter. At baseline, the median IgA, IgG, and IgM levels were 107 mg/dL (11-260), 834 mg/dL (387-3003), and 42 mg/dL (6-380), respectively, and remained generally unchanged at the end of treatment.

12.3 Pharmacokinetics

The pharmacokinetics (PK) of moxetumomab pasudotox-tdfk was studied in patients with HCL at doses ranging from 0.005 to 0.05 mg/kg (about 0.1 to 1.3 times the approved recommended dosage) administered intravenously over 30 minutes on Days 1, 3, and 5 of a 28-day cycle. Moxetumomab pasudotox-tdfk concentrations increased dose-proportionally over the studied dose range. The mean steady state moxetumomab pasudotox-tdfk exposures at the approved recommended dosages were 379 ng/mL (range: 20 to 862; SD: 262) for Cmax and 626 ng∙hour/mL (range: 5 to 1960; SD: 610) for AUC0-last. No systemic accumulation of moxetumomab pasudotox-tdfk was observed. Baseline CD19+ B cells were evaluated for association with the PK exposure and higher PK exposures were significantly associated with low baseline CD19+ counts (p < 0.001).

Distribution

The population PK model estimated mean volume of distribution of moxetumomab pasudotox-tdfk was 6.5 L (SD 2.4).

Elimination

The mean elimination half-life of moxetumomab pasudotox-tdfk was 1.4 hours (range: 0.8 to 1.8; SD: 0.35). The population PK model estimated mean systemic clearance of moxetumomab pasudotox-tdfk after the first dose of the first cycle was 25 L/hour (SD: 29.0) and after subsequent dosing was 4 L/hour (SD: 4.4).

Metabolism

The metabolic pathway of moxetumomab pasudotox-tdfk in humans is unknown, however, other protein therapeutics generally undergo proteolytic degradation into small peptides and amino acids via catabolic pathways.

Specific Populations

No clinically significant differences in the pharmacokinetics of moxetumomab pasudotox-tdfk were observed for age (36 to 84 years), sex, race (White and non-White), body weight (42 to 152 kg), mild hepatic impairment (total bilirubin ≤ upper limit of normal [ULN] and AST > ULN, or total bilirubin > 1 to 1.5 times ULN and any AST), mild renal impairment (CLcr 60-89 mL/min; n=40), or moderate renal impairment (CLcr 30-59 mL/min; n=4) based on population PK analysis.

The pharmacokinetics of moxetumomab pasudotox-tdfk in patients with moderate to severe hepatic impairment (total bilirubin > 1.5 ULN) or severe renal impairment (CrCl ≤ 29 mL/min) is unknown.

Anti-Product Antibody Formation Affecting PK

In patients who were ADA-positive with high titers, the presence of ADA post-baseline was associated with statistically significant (p < 0.05) lower PK exposure (Cmax) at later cycles (Cycle 3 and beyond).

13 NONCLINICAL TOXICOLOGY

13.1 Carcinogenesis, Mutagenesis, Impairment of Fertility

No studies have been conducted to assess the carcinogenic or genotoxic potential of moxetumomab pasudotox-tdfk. Animal fertility studies have not been conducted with moxetumomab pasudotox-tdfk.

13.2 Animal Toxicology and/or Pharmacology

At a human equivalent dose > 3 times the recommended dose, degeneration of heart tissue was observed in cynomolgus monkeys. At a human equivalent dose > 10 times the recommended dose, gliosis in the brain, axonal degeneration in the spinal cord, and body tremors were observed in cynomolgus monkeys.

14 CLINICAL STUDIES

The efficacy of LUMOXITI was based upon Study 1053 titled "A Pivotal Multicenter Trial of Moxetumomab Pasudotox in Relapsed/Refractory Hairy Cell Leukemia" (NCT01829711). Study 1053 was conducted in patients with histologically confirmed HCL or HCL variant with a need for therapy based on presence of cytopenias or splenomegaly and who had received prior treatment with at least 2 systemic therapies, including 1 purine nucleoside analog (PNA). Eligible patients had serum creatinine ≤ 1.5 mg/dL or creatinine clearance ≥ 60 mL/min as estimated by the Cockcroft Gault equation.

A total of 80 patients were enrolled; 77 with classic HCL and 3 with HCL variant. The median age was 60 years (range: 34 to 84) years, 79% were male, and 94% were Caucasian. At baseline, 98% of patients had an ECOG performance status of 0 or 1. The median number of prior treatments was 3 (range: 2 to 11); all patients received prior PNA therapy, including 29% in combination with rituximab. The most common other prior treatment regimens were rituximab monotherapy (51%), interferon-alpha (25%), and a BRAF inhibitor (18%). At baseline, 33% (26/80) of patients had low hemoglobin (< 10 g/dL), 68% (54/80) of patients had neutropenia (< 1000/mm^3), and 84% (67/80) patients had baseline platelet counts < 100,000/mm^3. About 35% of patients had enlarged spleens (≥ 14 cm, assessed by BICR) at baseline.

Patients received LUMOXITI 0.04 mg/kg as an intravenous infusion over 30 minutes on Days 1, 3, and 5 of each 28-day cycle for a maximum of 6 cycles or until documentation of complete response (CR), disease progression, or unacceptable toxicity. The median duration of follow-up was 16.7 months (range: 2 to 49). An independent review committee (IRC) performed efficacy evaluations using blood, bone marrow, and imaging criteria adapted from previous HCL studies and consensus guidelines.

Efficacy of LUMOXITI in HCL was evaluated by the IRC-assessed rate of durable CR, as confirmed by maintenance of hematologic remission (hemoglobin ≥ 11 g/dL, neutrophils ≥ 1500/mm^3, and platelets ≥ 100,000/mm^3 without transfusions or growth factor for at least 4 weeks) more than 180 days after IRC-assessed CR. The IRC-assessed durable CR rate was 30% (24/80 patients; 95% CI: 20, 41).

Additional efficacy outcome measures included overall response rate (ORR), CR, and duration of response (see Table 6).

Table 6: Additional Efficacy Results in Patients with HCL in Study 1053
 | Independent Review Committee (IRC) Assessed N=80
Overall Response Rate
Overall Response Rate [ORR defined as best overall response of CR or PR.] (%) [95% CI] | 75 [64, 84]
Complete Response [CR defined as clearing of the bone marrow of hairy cells by routine Hematoxylin & Eosin stain, radiologic resolution of pre-existing lymphadenopathy and/or organomegaly, and hematologic remission.] (%) [95% CI] | 41 [30, 53]
Partial Response [PR defined as ≥ 50% decrease or normalization (< 500/mm^3) in peripheral blood lymphocyte count, reduction of pre-existing lymphadenopathy and/or organomegaly, and hematologic remission.] (%) [95% CI] | 34 [24, 45]
Duration of Response
Median in months [range] | NR [0+ to 43+]
Duration of CR
Median in months [range] | NR [0+ to 40+]
CI=Confidence Interval; NR=Not Reached; + indicates censored observations

The median time to ORR and CR was 5.7 months (range: 1.8 to 12.9) and 5.9 months (range 1.8 to 13.2), respectively. Sixty-four patients (80%) had normalization of hematologic parameters and achieved hematologic remission, with a median time to hematologic remission of 1.1 months (range: 0.2 to 13) and with a median duration of hematologic remission not reached (range: 0.3 to 48.2+).

16 HOW SUPPLIED/STORAGE AND HANDLING

How Supplied

- LUMOXITI (moxetumomab pasudotox-tdfk) for injection is supplied as a sterile, preservative-free, white to off-white lyophilized cake or powder in a 1 mg single-dose vial. Each carton (NDC 73380-4700-1) contains one single-dose vial.
- IV Solution Stabilizer is supplied as a sterile, preservative-free, colorless to slightly yellow, clear solution free from visible particles in a 1 mL single-dose vial. The IV Solution Stabilizer is packaged separately from LUMOXITI. Each carton (NDC 73380-4715-9) contains one single-dose vial. Do not use the IV Solution Stabilizer to reconstitute LUMOXITI.

Only one vial of IV Solution Stabilizer should be used per administration of LUMOXITI.

Storage and Handling

Refrigerate LUMOXITI and IV Solution Stabilizer at 2°C to 8°C (36°F to 46°F), in original carton to protect from light. Do not freeze. Do not shake.

17 PATIENT COUNSELING INFORMATION

Advise the patient to read the FDA-approved patient labeling (Medication Guide).

Capillary Leak Syndrome

Advise patients on the risk of developing capillary leak syndrome. Advise patients to immediately report any symptoms suggestive of capillary leak syndrome, such as difficulty breathing, rapid weight gain, hypotension, or swelling of their arms, legs, and/or face to their healthcare provider for further evaluation [see Warnings and Precautions (5.1)].

Hemolytic Uremic Syndrome

Advise patients on the risk of developing hemolytic uremic syndrome. Advise patients on the importance of maintaining high fluid intake, and the need for frequent monitoring of blood chemistry values [see Warnings and Precautions (5.2)].

Renal Toxicity

Inform patients that taking LUMOXITI may cause decreased renal function. Advise patients to report any changes to urine output to their healthcare provider for further evaluation [see Warnings and Precautions (5.3) and Adverse Reactions (6.1)].

Infusion Related Reactions

Advise patients to contact their healthcare provider immediately for signs or symptoms of infusion related reactions [see Warnings and Precautions (5.4)].

Electrolyte Abnormalities

Advise patients to report symptoms of electrolyte abnormalities (e.g., muscle cramping, paresthesias, irregular or fast heartbeat, nausea, seizures) to their healthcare provider immediately [see Warnings and Precautions (5.5)].

Distributed by: Innate Pharma Inc., Rockville, MD 20850
Manufactured by: Innate Pharma Inc., Rockville, MD 20850
U.S. License No. 2206

LUMOXITI is a registered trademark of Innate Pharma.
© Innate Pharma 2020

MEDICATION GUIDE
LUMOXITI® (loo-MOCKS-eh-tee)
(moxetumomab pasudotox-tdfk)
for injection

What is the most important information I should know about LUMOXITI?
LUMOXITI can cause serious side effects, including:

- Capillary Leak Syndrome (CLS). LUMOXITI can cause fluid to leak from small blood vessels into your body's tissues. This condition is called "Capillary Leak Syndrome" (CLS). CLS can quickly cause you to have symptoms that may become life-threatening if not treated right away. Get emergency medical help right away if you develop any of the following symptoms of CLS:

- swelling of your face, arms, or legs
- fast weight gain (increase in 5.5 pounds from Day 1 of your current cycle)

- weakness or dizziness
- shortness of breath or trouble breathing
- cough
- low blood pressure

Your healthcare provider will check your weight and blood pressure before you receive each dose of LUMOXITI and as needed during treatment.

- Hemolytic Uremic Syndrome (HUS). Hemolytic uremic syndrome is a condition that affects your blood cells and kidneys and may be life-threatening if not treated right away. Get emergency medical help right away if you develop any of the following symptoms of HUS:

- decrease in the amount of urine or dark urine (tea-colored)
- unusual bleeding or bruising of your skin
- stomach pain
- vomiting
- fever

- feeling tired
- changes in mood or behavior
- confusion
- seizures
- shortness of breath
- fast heartbeat

Your healthcare provider will do blood tests to check your blood cells and kidneys before you receive each dose of LUMOXITI and during treatment as recommended by your healthcare provider.

If you develop any of these symptoms of CLS or HUS, your healthcare provider may monitor you in the hospital.
Getting medical treatment right away may help keep these problems from becoming more serious.
Your healthcare provider will check you for these problems during your treatment with LUMOXITI. Your healthcare provider may delay or completely stop treatment with LUMOXITI if you have severe side effects.
See "What are the possible side effects of LUMOXITI?" below for other side effects of LUMOXITI.

What is LUMOXITI?
LUMOXITI is a prescription medicine used to treat adults with hairy cell leukemia (HCL)

- that has come back or has not responded to previous treatment, and
- have received at least 2 other treatments, including a type of medicine called purine nucleoside analog (PNA).

It is not known if LUMOXITI is safe and effective in children.

Before you receive LUMOXITI, tell your healthcare provider about all your medical conditions, including if you:

- have had conditions that affect your blood and blood vessels called HUS or severe thrombotic microangiopathy (TMA)
- have kidney problems
- are pregnant or plan to become pregnant. LUMOXITI may harm your unborn baby.
  - If you are a female who can become pregnant, you should use effective birth control during treatment with LUMOXITI and for at least 30 days after your last dose of LUMOXITI.
  - If you are a female who can become pregnant, your healthcare provider will perform a pregnancy test before you start treatment with LUMOXITI.
  - Tell your healthcare provider right away if you become pregnant during treatment with LUMOXITI.
- are breastfeeding or plan to breastfeed. It is not known if LUMOXITI passes into your breast milk. You and your healthcare provider should decide if you will receive LUMOXITI or breastfeed. You should not do both.

Tell your healthcare provider about all the medicines you take, including prescription and over-the-counter medicines, vitamins, and herbal supplements.
Know the medicines you take. Keep a list of your medicines with you and show it to your healthcare provider when you get a new medicine.

How will I receive LUMOXITI?

- Your healthcare provider will give you LUMOXITI into your vein through an intravenous (IV) line over 30 minutes.
- LUMOXITI is usually given on Day 1, Day 3, and Day 5 of a 28-day treatment cycle. This is 1 treatment cycle. You may receive up to 6 treatment cycles.
- Your healthcare provider will give you medicines and IV fluids before and after your infusions.
- It is important for you to drink the additional prescribed amount of fluids (water, milk, or juice) of up to twelve 8-oz glasses every 24 hours on Days 1 through 8 of each 28-day treatment cycle when you receive LUMOXITI infusions.
- Your healthcare provider will decide how many treatment cycles you need.
- If you miss any appointments, call your healthcare provider as soon as possible to reschedule your appointment.

What are the possible side effects of LUMOXITI?
LUMOXITI can cause serious side effects, including:

- See "What is the most important information I should know about LUMOXITI?"
- Kidney problems. LUMOXITI may cause kidney problems. People who have HUS, are 65 years of age or older, or those who have kidney problems before starting treatment with LUMOXITI may have an increased risk of worse kidney problems after treatment with LUMOXITI. Tell your healthcare provider right away if you have any changes in the amount you urinate. Your healthcare provider will do tests to check your kidneys before you receive each dose of LUMOXITI and as needed during treatment. Your healthcare provider may delay your treatment with LUMOXITI if you have severe kidney problems.
- Infusion reactions. LUMOXITI can cause infusion reactions that are common but can also be serious. Infusion reactions may happen on the day you receive your LUMOXITI infusion. Signs and symptoms of infusion reactions may include:

- chills
- cough
- dizziness
- shortness of breath or wheezing
- feeling hot or flushing
- fast heartbeat

- headache
- changes in blood pressure
- muscle pain
- nausea
- fever
- vomiting

Your healthcare provider may give you medicines to take before and after each LUMOXITI infusion.

- Electrolyte problems. Tell your healthcare provider if you get any of the following symptoms of electrolyte problems:

- muscle cramps
- numbness or tingling
- abnormal or fast heartbeat

- nausea
- seizures

Your healthcare provider will do blood tests to check your electrolytes before you receive each dose of LUMOXITI and during treatment as recommended by your healthcare provider.

The most common side effects of LUMOXITI include:

- swelling in your face, arms, or legs
- nausea
- feeling tired
- headache

- fever
- constipation
- low red blood cells (anemia)
- diarrhea

These are not all the possible side effects of LUMOXITI.
Call your doctor for medical advice about side effects. You may report side effects to FDA at 1-800-FDA-1088.

General information about the safe and effective use of LUMOXITI.
Medicines are sometimes prescribed for purposes other than those listed in a Medication Guide. You can ask your pharmacist or healthcare provider for information about LUMOXITI that is written for health professionals.

What are the ingredients in LUMOXITI?
Active ingredient: moxetumomab pasudotox-tdfk
Inactive ingredients: glycine, polysorbate 80, sodium phosphate monobasic monohydrate, sucrose, and sodium hydroxide
Inactive ingredients of IV Solution Stabilizer: citric acid monohydrate, polysorbate 80, sodium citrate dihydrate, Water for Injection, USP
LUMOXITI is a registered trademark of Innate Pharma.© Innate Pharma 2020
Distributed by: Innate Pharma Inc., Rockville, MD 20850
Manufactured by: Innate Pharma Inc., Rockville, MD 20850; U.S. License No. 2206
For more information, go to www.LUMOXITI.com or call 1-888-501-0998.

This Medication Guide has been approved by the U.S. Food and Drug Administration.

Issued: August 2020

INSTRUCTIONS FOR USE

LUMOXITI® (moxetumomab pasudotox-tdfk)
for injection

Healthcare Provider Instructions for Use

Important Information

Read the following instructions before reconstitution, dilution, and administration of LUMOXITI.

- LUMOXITI must be prepared by a healthcare professional using proper aseptic technique.
- Do not freeze or shake LUMOXITI or IV Solution Stabilizer.
- Provide each patient the Medication Guide packaged with LUMOXITI prior to each treatment cycle to inform them of the risks and benefits of LUMOXITI.
- See Full Prescribing Information for more information on LUMOXITI.

For questions, call Innate Pharma at 1-888-501-0998.

How Supplied

- LUMOXITI and IV Solution Stabilizer are packaged separately.
- Prior to preparation, LUMOXITI and IV Solution Stabilizer should be stored at 2°C to 8°C (36°F to 46°F) in original cartons to protect from light.

LUMOXITI (moxetumomab pasudotox-tdfk)

- Each single-dose vial supplies LUMOXITI 1 mg/vial (moxetumomab pasudotox-tdfk) for injection as a lyophilized cake or powder for reconstitution and dilution prior to intravenous infusion.
  - Multiple vials of LUMOXITI may be required to administer a single dose (See Step 1: Calculate Dose).
  - Reconstitute LUMOXITI vials with Sterile Water for Injection, USP only (not supplied).

IV Solution Stabilizer

- Each single-dose vial contains 1 mL IV Solution Stabilizer.
- Only one vial of IV Solution Stabilizer is needed per administration of LUMOXITI, regardless of the number of vials of LUMOXITI used to prepare the infusion.
- Do not use IV Solution Stabilizer to reconstitute LUMOXITI.
- Do not flush IV lines with IV Solution Stabilizer.

Storage and Handling of Reconstituted and Diluted LUMOXITI

Table 1. Storage Times and Conditions for Reconstituted and Diluted LUMOXITI Solution
Reconstituted Solution | Diluted LUMOXITI Solution in Infusion Bag
Reconstituted Solution | After Dilution | Administration
LUMOXITI does not contain bacteriostatic preservatives. Use reconstituted solution immediately. DO NOT STORE reconstituted LUMOXITI vials. | Use diluted solution immediately or after storage at room temperature (20°C to 25°C; 68°F to 77°F) for up to 4 hours or store refrigerated at 2°C to 8°C (36°F to 46°F) for up to 24 hours. PROTECT FROM LIGHT. DO NOT FREEZE. DO NOT SHAKE. | If the diluted solution is refrigerated (2°C to 8°C; 36°F to 46°F), allow it to equilibrate at room temperature (20°C to 25°C; 68°F to 77°F) for no more than 4 hours prior to administration. Administer diluted solution within 24 hours of reconstitution as a 30-minute infusion. PROTECT FROM LIGHT.

Step 1: Calculate Dose

Calculate the dose (mg) and the number of LUMOXITI vials (1 mg/vial) to be reconstituted. The final concentration of the reconstituted LUMOXITI solution is 1 mg/mL.

- Individualize dosing based on the patient's actual body weight prior to the first dose of the first treatment cycle.
  - A change in dose should only be made between cycles when a change in weight of greater than 10% is observed from the weight used to calculate the first dose of the first treatment cycle. No change in dose should be made during a particular cycle.
- Do not round down the dose for partial vials.

Step 2: Gather Supplies

- LUMOXITI 1 mg/vial (number of vials to be reconstituted are based on Step 1)
- 1 vial of IV Solution Stabilizer (packaged separately)
- alcohol swabs
- 1 infusion bag containing 50 mL of 0.9% Sodium Chloride Injection, USP
- Sterile Water for Injection, USP
- syringes and needles

Step 3: Reconstitution

Reconstitute each LUMOXITI vial with 1.1 mL Sterile Water for Injection, USP using aseptic technique.

- Direct the Sterile Water for Injection, USP slowly along the walls of the LUMOXITI vial and not directly at the lyophilized cake or powder (see figure below).

- Do not reconstitute LUMOXITI vials with the IV Solution Stabilizer.
- Gently swirl the vial until completely dissolved. Invert the vial to ensure all cake or powder in the vial is dissolved. Do not shake.

Visually inspect that the reconstituted solution is clear to slightly opalescent, colorless to slightly yellow, and free from visible particles.

- Do not use if solution is cloudy, discolored, or contains any particles.

The resulting 1 mg/mL solution allows a withdrawal volume of 1 mL.

Use reconstituted solution immediately. Do not store reconstituted LUMOXITI vials. See Table 1 for storage times and conditions for the reconstituted solution.

Step 4: Preparation of Infusion Bag with IV Solution Stabilizer

Obtain a 50 mL 0.9% Sodium Chloride Injection, USP infusion bag.

Only one vial of IV Solution Stabilizer is needed per administration of LUMOXITI, regardless of the number of vials of LUMOXITI used to prepare the infusion.

- Add 1 mL IV Solution Stabilizer to the infusion bag containing 50 mL 0.9% Sodium Chloride Injection, USP.
- Gently invert the bag to mix the solution. Do not shake.

Step 5: Dilution

Slowly withdraw the required volume of reconstituted LUMOXITI solution needed from each vial, per the calculated dose based on the patient's actual body weight (kg).

- Inject LUMOXITI into the infusion bag containing 50 mL 0.9% Sodium Chloride Injection, USP and 1 mL IV Solution Stabilizer.
- Gently invert the bag to mix the solution. Do not shake.
- Discard any partially used or empty vials of LUMOXITI and IV Solution Stabilizer.
- See Table 1 for storage times and conditions for the diluted solution.

Step 6: Intravenous Hydration and Pre-infusion Medications

Administer intravenous hydration and premedication to the patient.

- Intravenously administer 1 L of isotonic solution (e.g. 5% Dextrose Injection, USP and 0.45% or 0.9% Sodium Chloride Injection, USP) over 2 to 4 hours before each LUMOXITI infusion. Administer 0.5 L to patients under 50 kg.
- Premedicate 30 to 90 minutes prior to each LUMOXITI infusion with an antihistamine (e.g. hydroxyzine or diphenhydramine), acetaminophen, and a histamine-2 receptor antagonist (e.g. ranitidine, famotidine, or cimetidine).

Step 7: Administration

Infuse the diluted LUMOXITI solution intravenously over 30 minutes.

- Do not mix LUMOXITI, or administer as an infusion with other medicinal products.
- After the infusion, flush the intravenous administration line with of 0.9% Sodium Chloride Injection, USP at the same rate as the infusion. This ensures that the full LUMOXITI dose is delivered.

Step 8: Post-infusion Medications

Administer post-infusion medications.

- Intravenously administer 1 L of isotonic solution (e.g. 5% Dextrose Injection, USP and 0.45% or 0.9% Sodium Chloride Injection, USP) over 2 to 4 hours after each LUMOXITI infusion. Administer 0.5 L to patients under 50 kg.
- Consider oral antihistamines and acetaminophen for up to 24 hours following LUMOXITI infusions.
- Consider oral corticosteroid (e.g. 4 mg dexamethasone) to manage nausea and vomiting.

Maintain adequate oral fluid intake.

- Advise all patients to adequately hydrate with up to 3 L (twelve 8-oz glasses) of oral fluids (e.g. water, milk, or juice) per 24 hours on Days 1 through 8 of each 28-day treatment cycle. In patients under 50 kg, up to 2 L (eight 8-oz glasses) per 24-hour period is recommended.

Consider low-dose aspirin on Days 1 through 8 of each 28-day treatment cycle.

This Healthcare Provider Instructions for Use has been approved by the U.S. Food and Drug Administration.

LUMOXITI is a registered trademark of Innate Pharma. © Innate Pharma 2020
Distributed by: Innate Pharma Inc., Rockville, MD 20850
Manufactured by: Innate Pharma Inc., Rockville, MD 20850; U.S. License No. 2206

For more information, go to www.LUMOXITI.com or call 1-888-501-0998.
Revised: 8/2020

PRINCIPAL DISPLAY PANEL - 1 mg Vial Carton

NDC 73380-4700-1
Rx only

LUMOXITI®
(moxetumomab pasudotox-tdfk)
for Injection

1 mg/vial

For Intravenous Infusion Only After Reconstitution and Dilution

ATTENTION PHARMACIST:
Use ONLY with IV Solution Stabilizer for LUMOXITI®;
packaged separately, to prepare the infusion
bag prior to adding reconstituted LUMOXITI®

Keep vial in original carton to protect from light.
No preservatives.

Dispense the accompanying
Medication Guide to each patient.

One single-dose vial
Discard unused portion

innate pharma

PRINCIPAL DISPLAY PANEL - 1 mL Vial Carton

NDC 73380-4715-9
Rx only

IV Solution Stabilizer for
LUMOXITI®

1 mL

ATTENTION PHARMACIST: Use ONLY to prepare
the infusion bag prior to adding reconstituted
LUMOXITI®, packaged separately.

One single-dose vial. Discard unused portion.

DO NOT use IV Solution Stabilizer to reconstitute
LUMOXITI® vials.

Dosage: See LUMOXITI® prescribing information and the
Healthcare Provider Instructions for Use for dosage,
preparation and administration.

Do not use if vial seal is broken or missing.

innate pharma